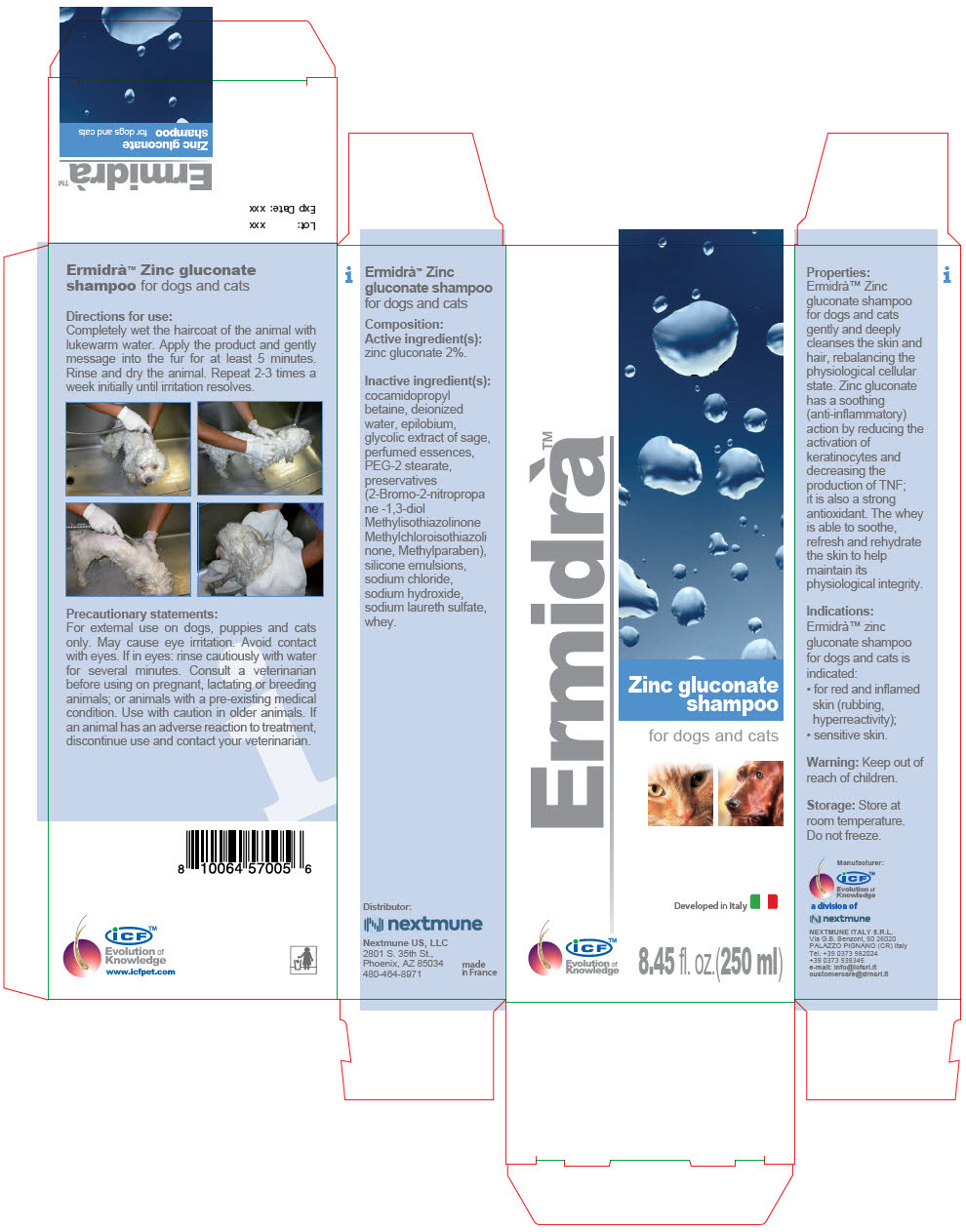 DRUG LABEL: ERMIDRA
NDC: 86127-006 | Form: SHAMPOO
Manufacturer: Nextmune AB
Category: animal | Type: OTC ANIMAL DRUG LABEL
Date: 20220526

ACTIVE INGREDIENTS: ZINC GLUCONATE 20 mg/1 mL
INACTIVE INGREDIENTS: water; WHEY; SODIUM C12-14 PARETH-3 SULFATE; COCAMIDOPROPYL BETAINE; PEG-2 STEARATE; SAGE; METHYLPARABEN; BRONOPOL; METHYLISOTHIAZOLINONE; METHYLCHLOROISOTHIAZOLINONE; EPILOBIUM ANGUSTIFOLIUM LEAF; SODIUM HYDROXIDE; SODIUM CHLORIDE

ERMIDRÀ™ SHAMPOO

VETERINARY INDICATIONS

Ermidrà™ Zinc gluconate shampoo for dogs and cats

Composition:

Active ingredient(s):

zinc gluconate 2%.

Inactive ingredient(s):

cocamidopropyl betaine, deionized water, epilobium, glycolic extract of sage, perfumed essences, PEG-2 stearate, preservatives (2-Bromo-2-nitropropane -1,3-diol Methylisothiazolinone Methylchloroisothiazolinone, Methylparaben), silicone emulsions, sodium chloride, sodium hydroxide, sodium laureth sulfate, whey.

Directions for use:

Completely wet the haircoat of the animal with lukewarm water. Apply the product and gently message into the fur for at least 5 minutes. Rinse and dry the animal. Repeat 2-3 times a week initially until irritation resolves.

Precautionary statements:

For external use on dogs, puppies and cats only. May cause eye irritation. Avoid contact with eyes. If in eyes: rinse cautiously with water for several minutes. Consult a veterinarian before using on pregnant, lactating or breeding animals; or animals with a pre-existing medical condition. Use with caution in older animals. If an animal has an adverse reaction to treatment, discontinue use and contact your veterinarian.

Properties:

Ermidrà™ Zinc gluconate shampoo for dogs and cats gently and deeply cleanses the skin and hair, rebalancing the physiological cellular state. Zinc gluconate has a soothing (anti-inflammatory) action by reducing the activation of keratinocytes and decreasing the production of TNF; it is also a strong antioxidant. The whey is able to soothe, refresh and rehydrate the skin to help maintain its physiological integrity.

Indications:

Ermidrà™ zinc gluconate shampoo for dogs and cats is indicated:

- for red and inflamed skin (rubbing, hyperreactivity);
- sensitive skin.

Warning: Keep out of reach of children.

Storage: Store at room temperature. Do not freeze.

iCF™
Evolution of
Knowledge
www.icfpet.com

Distributor:
Nextmune US, LLC
2801 S. 35th St.,
Phoenix, AZ 85034
480-464-8971

made
in France

Manufacturer
iCF™
Evolution of
Knowledge

a division of

NEXTMUNE ITALY S.R.L.
Via G.B. Benzoni, 50 26020
PALAZZO PIGNANO (CR) Italy
Tel. +39 0373 982024
+39 0373 938345
e-mail: info@icfsrl.it
customercare@drnsrl.it

PRINCIPAL DISPLAY PANEL - 250 ml Bottle Carton

Ermidrà™

Zinc gluconate
shampoo
for dogs and cats

Developed in Italy

iCF™
Evolution of
Knowledge

8.45 fl. oz.(250 ml)